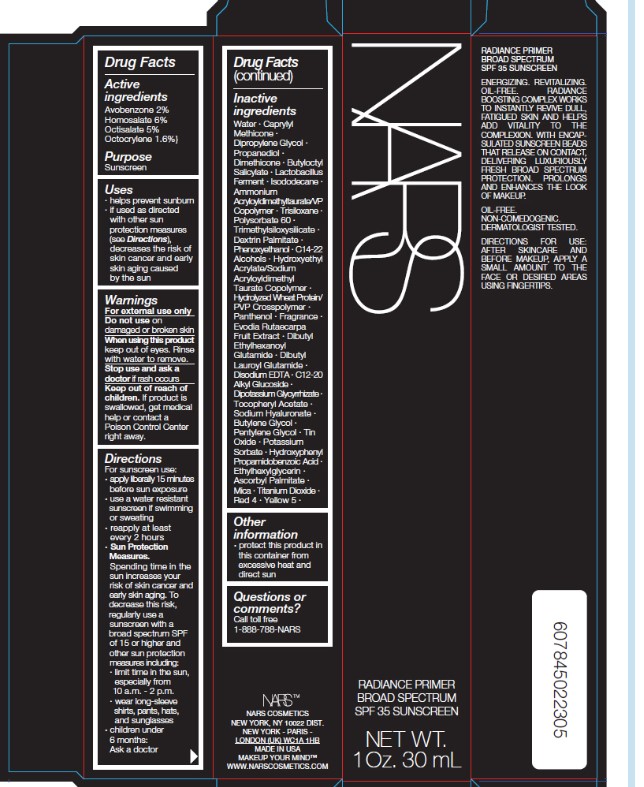 DRUG LABEL: NARS Radiance Primer Broad Spectrum SPF 35 Sunscreen
NDC: 68577-159 | Form: LOTION
Manufacturer: COSMAX USA, CORPORATION
Category: otc | Type: HUMAN OTC DRUG LABEL
Date: 20241226

ACTIVE INGREDIENTS: AVOBENZONE 2 mg/100 mg; HOMOSALATE 6 mg/100 mg; OCTOCRYLENE 1.6 mg/100 mg; OCTISALATE 5 mg/100 mg
INACTIVE INGREDIENTS: FD&C RED NO. 4; GLYCYRRHIZINATE DIPOTASSIUM; PENTYLENE GLYCOL; ASCORBYL PALMITATE; DEXTRIN PALMITATE (CORN; 20000 MW); ISODODECANE; .ALPHA.-TOCOPHEROL ACETATE; DIBUTYL LAUROYL GLUTAMIDE; HYALURONATE SODIUM; DIMETHICONE; TRIMETHYLSILOXYSILICATE (M/Q 0.6-0.8); PROPANEDIOL; STANNIC OXIDE; C12-20 ALKYL GLUCOSIDE; CAPRYLYL TRISILOXANE; WATER; TRISILOXANE; PHENOXYETHANOL; HYDROXYETHYL ACRYLATE/SODIUM ACRYLOYLDIMETHYL TAURATE COPOLYMER (45000 MPA.S AT 1%); PANTHENOL; EDETATE DISODIUM; BUTYLENE GLYCOL; POTASSIUM SORBATE; ETHYLHEXYLGLYCERIN; LIMOSILACTOBACILLUS REUTERI; C14-22 ALCOHOLS; TETRADIUM RUTICARPUM FRUIT; AMMONIUM ACRYLOYLDIMETHYLTAURATE/VP COPOLYMER; HYDROXYPHENYL PROPAMIDOBENZOIC ACID; DIBUTYL ETHYLHEXANOYL GLUTAMIDE; FD&C YELLOW NO. 5; MICA; POLYSORBATE 60; DIPROPYLENE GLYCOL; TITANIUM DIOXIDE

NARS Radiance Primer Broad Spectrum SPF 35 Sunscreen

Active Ingredients

Homosalate 6%

Octisalate 5%

Octocrylene 1.6%

Avobenzone 2%

Purpose

Sunscreen

USES

- helps prevent sunburn
- if used as directed with other sun protection measures (see Directions), decreases the risk of skin cancer and early skin aging cause by the sun

Warnings

For extenal use only

Do not useon damaged or broken skin

WHEN USING

When using this productkeep out of eyes. Rinse with water to remove.

Stop use and ask a doctor ifrash occurs

Keep out of reach of children.If swallowed, get medical help or contact a Poison Control Center right away.

DIRECTIONS

For sunscreen use:

- apply liberally 15 minutes before sun exposure
- use a water resistant sunscreen if swimming or sweating
- reapply at least every 2 hours

Sun Protection Measures.
Spending time in the sun increases your risk of skin cancer and early skin aging. To decrease this risk, regularly use a sunscreen with a broad spectrum SPF of 15 or higher and other sun protection measures including:

limit time in the sun, especially from 10 a.m. - 2 p.m.
wear long-sleeve shirts, pants, hats, and sunglasses

- children under 6 months: Ask a doctor

Inactive ingredients:

Water ∙ Caprylyl Methicone ∙ Dipropylene Glycol ∙ Propanediol ∙ Dimethicone ∙ Butyloctyl Salicylate ∙ Lactobacillus Ferment ∙ Isododecane ∙ Ammonium Acryloyldimethyltaurate/VP Copolymer ∙ Trisiloxane ∙ Polysorbate 60 ∙ Trimethylsiloxysilicate ∙ Dextrin Palmitate ∙ Phenoxyethanol ∙ C14-22 Alcohols ∙ Hydroxyethyl Acrylate/Sodium Acryloyldimethyl Taurate Copolymer ∙ Hydrolyzed Wheat Protein/PVP Crosspolymer ∙ Panthenol ∙ Fragrance ∙ Evodia Rutaecarpa Fruit Extract ∙ Dibutyl Ethylhexanoyl Glutamide ∙ Dibutyl Lauroyl Glutamide ∙ Disodium EDTA ∙ C12-20 Alkyl Glucoside ∙ Dipotassium Glycyrrhizate ∙ Tocopheryl Acetate ∙ Sodium Hyaluronate ∙ Butylene Glycol ∙ Pentylene Glycol ∙ Tin Oxide ∙ Potassium Sorbate ∙ Hydroxyphenyl Propamidobenzoic Acid ∙ Ethylhexylglycerin ∙ Ascorbyl Palmitate ∙ Mica ∙ Titanium Dioxide ∙ Red 4 ∙ Yellow 5 ∙

OTHER INFORMATION

- Protect the product in this container from excessive heat and direct sun

QUESTIONS or COMMENTS

Call toll free 1-888-788-NARS

PACKAGE LABEL

Packaging